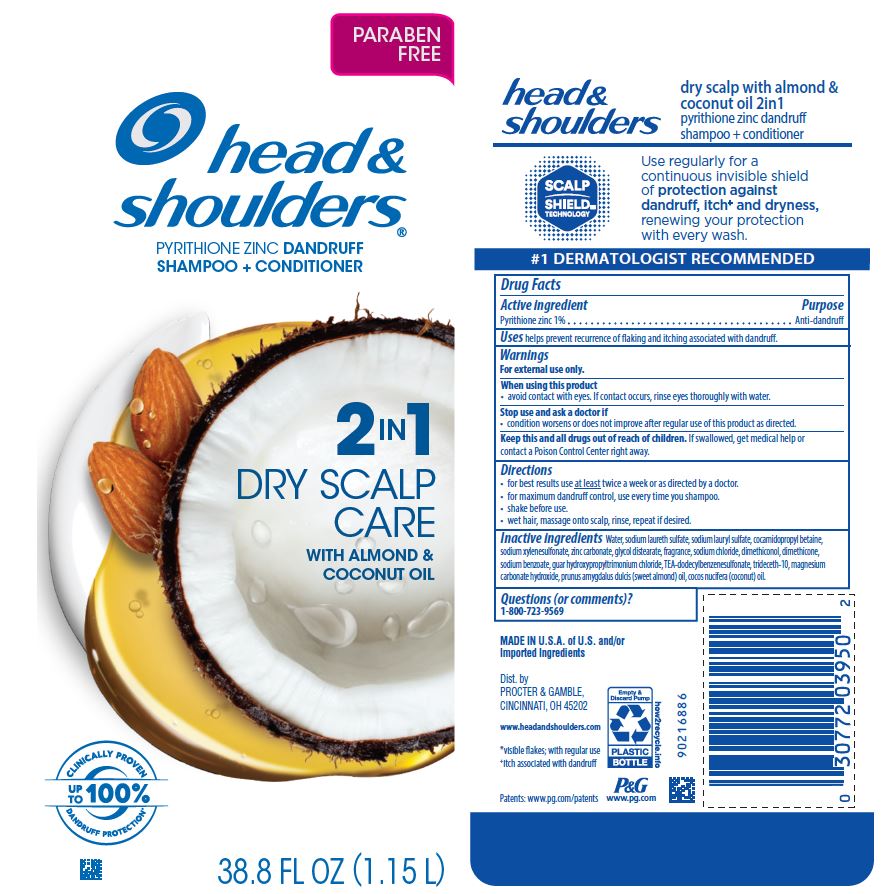 DRUG LABEL: Head and Shoulders 2in1 Dry Scalp Care with Almond and Coconut Oil
NDC: 69423-648 | Form: SHAMPOO
Manufacturer: The Procter & Gamble Manufacturing Company
Category: otc | Type: HUMAN OTC DRUG LABEL
Date: 20251231

ACTIVE INGREDIENTS: PYRITHIONE ZINC 1 g/100 mL
INACTIVE INGREDIENTS: MAGNESIUM CARBONATE HYDROXIDE; COCONUT OIL; DIMETHICONOL GUM; TRIDECETH-10; ALMOND OIL; TRIETHANOLAMINE DODECYLBENZENESULFONATE; SODIUM LAURYL SULFATE; GUAR HYDROXYPROPYLTRIMONIUM CHLORIDE (1.7 SUBSTITUENTS PER SACCHARIDE); WATER; SODIUM LAURETH SULFATE; DIMETHICONE; ZINC CARBONATE; GLYCOL DISTEARATE; SODIUM XYLENESULFONATE; COCAMIDOPROPYL BETAINE; SODIUM CHLORIDE; SODIUM BENZOATE

Head and Shoulders® 2in1 Dry Scalp Care with Almond & Coconut Oil Shampoo

Drug Facts

Active ingredient

Pyrithione zinc 1%

Purpose

Anti-dandruff

Uses

helps prevent recurrence of flaking and itching associated with dandruff.

Warnings

For external use only.

When using this product

- avoid contact with eyes. If contact occurs, rinse eyes thoroughly with water.

Stop use and ask a doctor if

- condition worsens or does not improve after regular use of this product as directed.

KEEP OUT OF REACH OF CHILDREN

Keep this and all drugs out of reach of children. If swallowed, get medical help or contact a Poison Control Center right away.

Directions

- for best results use at least twice a week or as directed by a doctor.
- for maximum dandruff control, use every time you shampoo.
- shake before use.
- wet hair, massage onto scalp, rinse, repeat if desired.

Inactive ingredients

Water, sodium laureth sulfate, sodium lauryl sulfate, cocamidopropyl betaine, sodium xylenesulfonate, zinc carbonate, glycol distearate, fragrance, sodium chloride, dimethiconol, dimethicone, sodium benzoate, guar hydroxypropyltrimoniumchloride, TEA-dodecylbenzenesulfonate, trideceth-10, magnesium carbonate hydroxide, prunus amygdalus dulcis (sweet almond) oil, cocos nucifera (coconut) oil

Questions (or comments)?

1-800-723-9569

MADE IN U.S.A. of U.S. and/or Imported Ingredients

Dist. by PROCTER & GAMBLE,
CINCINNATI, OH 45202

PRINCIPAL DISPLAY PANEL - 1.15L Bottle Label

head &
shoulders ®

PYRITHIONE ZINC DANDRUFF

SHAMPOO + CONDITIONER

2in1

DRY SCALP

CARE

WITH ALMOND &

COCONUT OIL

38.8 FL OZ (1.15L)